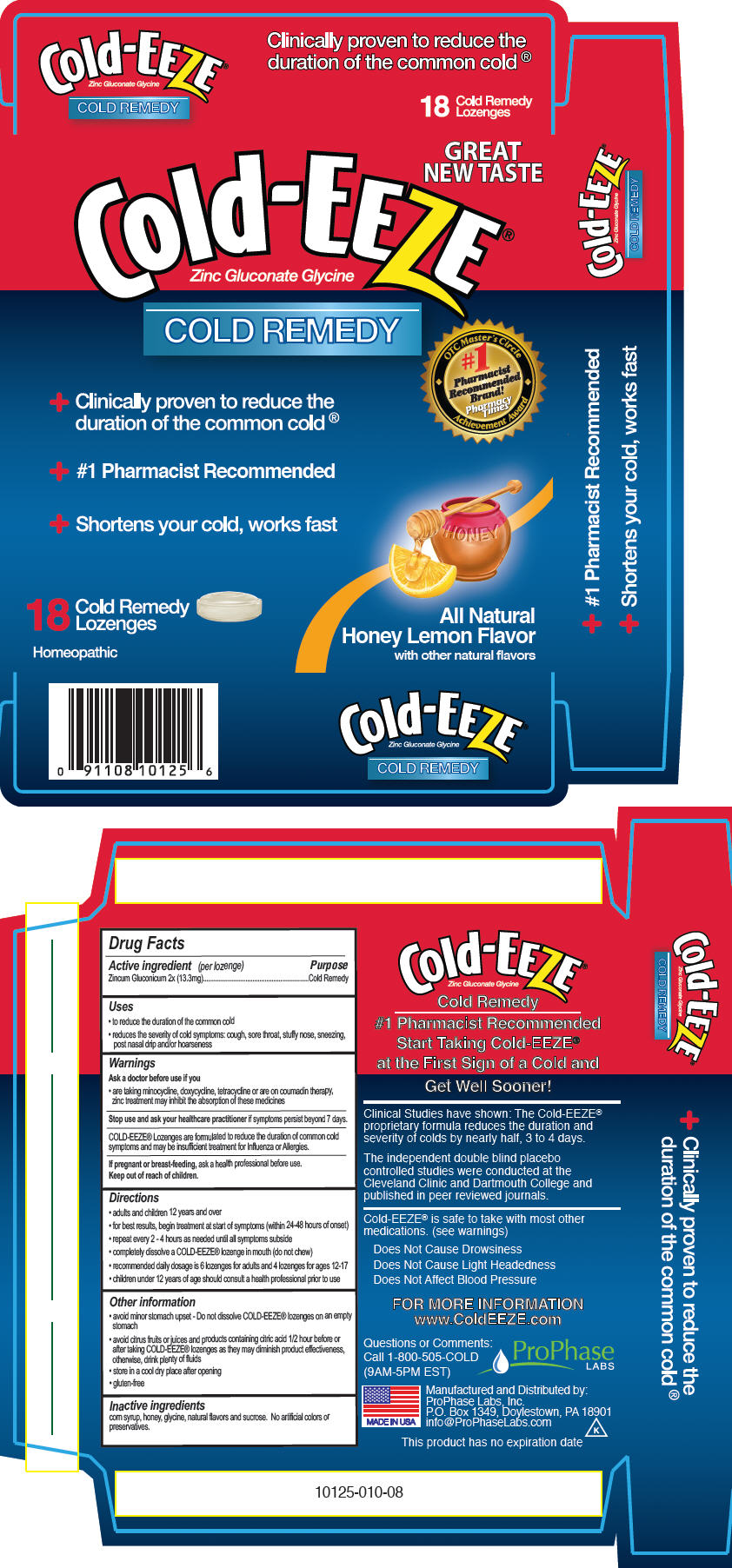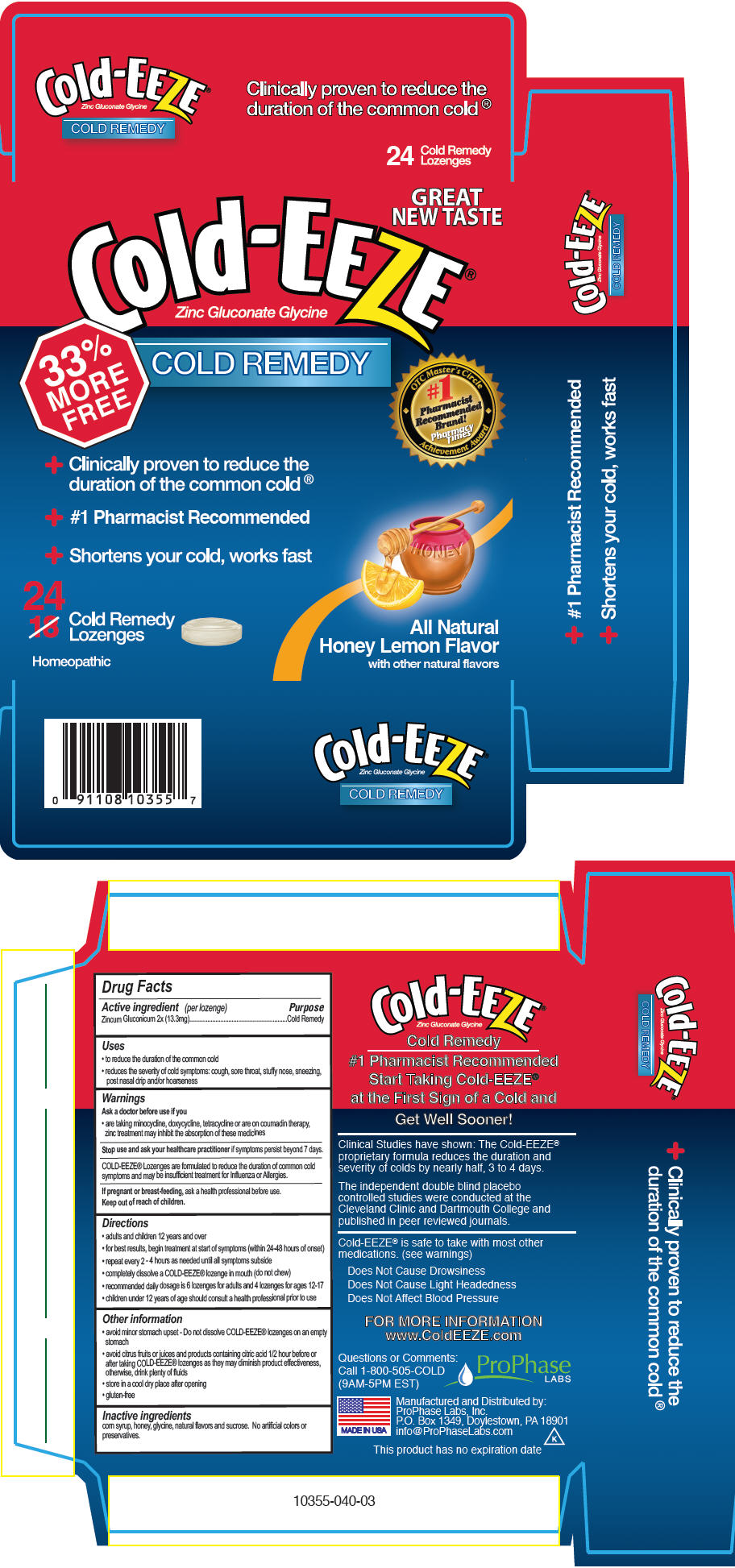 DRUG LABEL: Cold-EEZE
NDC: 61941-0021 | Form: LOZENGE
Manufacturer: ProPhase Labs, Inc.
Category: homeopathic | Type: HUMAN OTC DRUG LABEL
Date: 20110330

ACTIVE INGREDIENTS: Zinc Gluconate 2 [hp_X]/1 1
INACTIVE INGREDIENTS: Corn Syrup; Glycine; Sucrose; Honey

Cold-EEZE®
Honey Lemon

Drug Facts

Active ingredient (per lozenge)

Zincum Gluconicum 2x (13.3mg)

Purpose

Cold Remedy

Uses

- to reduce the duration of the common cold
- reduces the severity of cold symptoms: cough, sore throat, stuffy nose, sneezing, post nasal drip and/or hoarseness

Warnings

Ask a doctor before use if you

- are taking minocycline, doxycycline, tetracycline or are on coumadin therapy, zinc treatment may inhibit the absorption of these medicines

Stop use and ask your healthcare practitioner if symptoms persist beyond 7 days.

WHEN USING

COLD-EEZE® Lozenges are formulated to reduce the duration of common cold symptoms and may be insufficient treatment for Influenza or Allergies.

PREGNANCY OR BREAST FEEDING

If pregnant or breast-feeding, ask a health professional before use.

Keep out of reach of children.

Directions

- adults and children 12 years and over
- for best results, begin treatment at start of symptoms (within 24-48 hours of onset)
- repeat every 2 - 4 hours as needed until all symptoms subside
- completely dissolve a COLD-EEZE® lozenge in mouth (do not chew)
- recommended daily dosage is 6 lozenges for adults and 4 lozenges for ages 12-17
- children under 12 years of age should consult a health professional prior to use

Other information

- avoid minor stomach upset - Do not dissolve COLD-EEZE® lozenges on an empty stomach
- avoid citrus fruits or juices and products containing citric acid 1/2 hour before or after taking COLD-EEZE® lozenges as they may diminish product effectiveness, otherwise, drink plenty of fluids
- store in a cool dry place after opening
- gluten-free

Inactive ingredients

corn syrup, honey, glycine, natural flavors and sucrose. No artificial colors or preservatives.

Questions or Comments

Call 1-800-505-COLD
(9AM-5PM EST)

PRINCIPAL DISPLAY PANEL - 18 Lozenge Package

GREAT
NEW TASTE

Cold-EEZE®
Zinc Gluconate Glycine

COLD REMEDY

OTC Master's Circle
Achievement Award
#1
Pharmacist
Recommended
Brand!
Pharmacy
Times

+ Clinically proven to reduce the
  duration of the common cold®
+ #1 Pharmacist Recommended
+ Shortens your cold, works fast

18
Cold Remedy
Lozenges

Homeopathic

All Natural
Honey Lemon Flavor
with other natural flavors

PRINCIPAL DISPLAY PANEL - 24 Lozenge Package

GREAT
NEW TASTE

Cold-EEZE®
Zinc Gluconate Glycine

33%
MORE
FREE

COLD REMEDY

OTC Master's Circle
Achievement Award
#1
Pharmacist
Recommended
Brand!
Pharmacy
Times

+ Clinically proven to reduce the
  duration of the common cold®
+ #1 Pharmacist Recommended
+ Shortens your cold, works fast

24
Cold Remedy
Lozenges

Homeopathic

All Natural
Honey Lemon Flavor
with other natural flavors